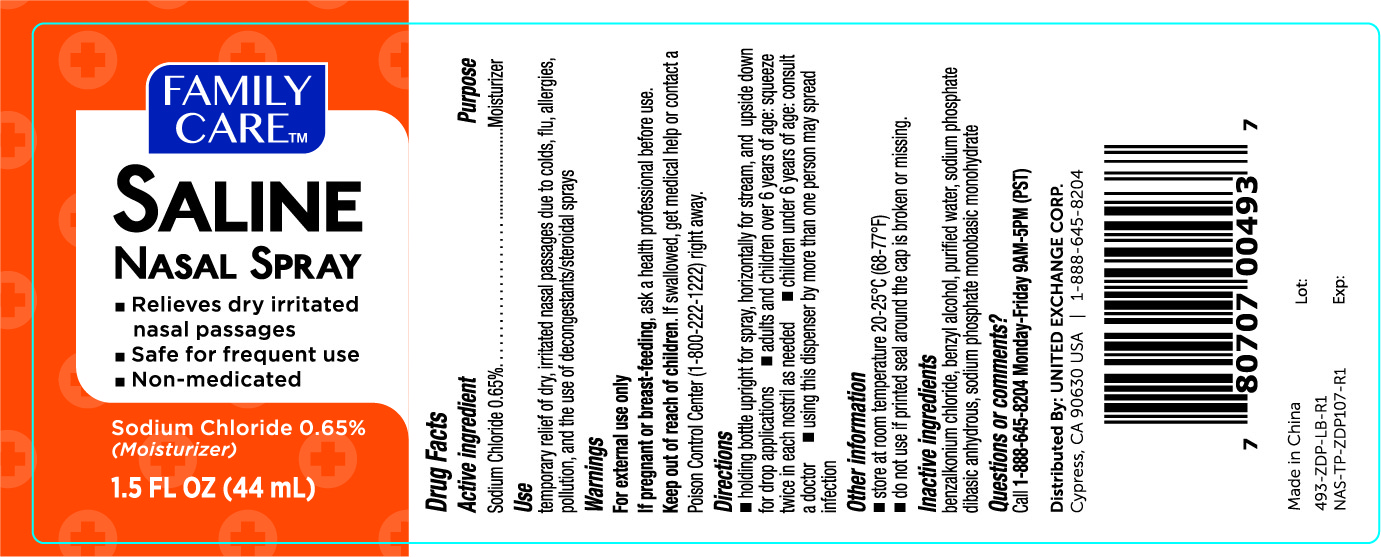 DRUG LABEL: Family Care Saline
NDC: 65923-493 | Form: SPRAY
Manufacturer: United Exchange Corp.
Category: otc | Type: HUMAN OTC DRUG LABEL
Date: 20251031

ACTIVE INGREDIENTS: SODIUM CHLORIDE 6.5 mg/1 mL
INACTIVE INGREDIENTS: SODIUM PHOSPHATE DIBASIC DIHYDRATE; SODIUM PHOSPHATE, MONOBASIC, MONOHYDRATE; BENZYL ALCOHOL; WATER; BENZALKONIUM CHLORIDE

Family Care Saline Nasal Spray 1.5oz 493

Active ingredient Purpose

Sodium Chloride 0.65%......................Moisturizer

Use

temporary relief of dry, irritated nasal passages due to colds, flu, allergies, pollution, and the use of decongestants/steroidal sprays

Warnings

For external use only

PREGNANCY OR BREAST FEEDING

If pregnant or breast-feeding, ask a health professional before use.

Keep out of reach of children. If swallowed, get medical help or contact a Poison Control Center (1-800-222-1222) right away.

Directions

- holding bottle upright for spray, horizontally for stream, and upside down for drop applications
- adults and children under 6 years of age: squeeze twice in each nostril as needed
- children under 6 years of age: consult a doctor
- using this dispenser by more than one person may spread infection

Other information

- store at room temperature 20-25°C (68-77°F)
- do not use if printed seal around the cap is broken or missing

Inactive ingredients

benzalkonium chloride, benzyl alcohol, purified water, sodium phosphate dibasic anhydrous, sodium phosphate monobasic monohydrate

DOSAGE AND ADMINISTRATION

Distributed by: United Exchange Corp.

Cypress, CA 90630 USA

Made in China